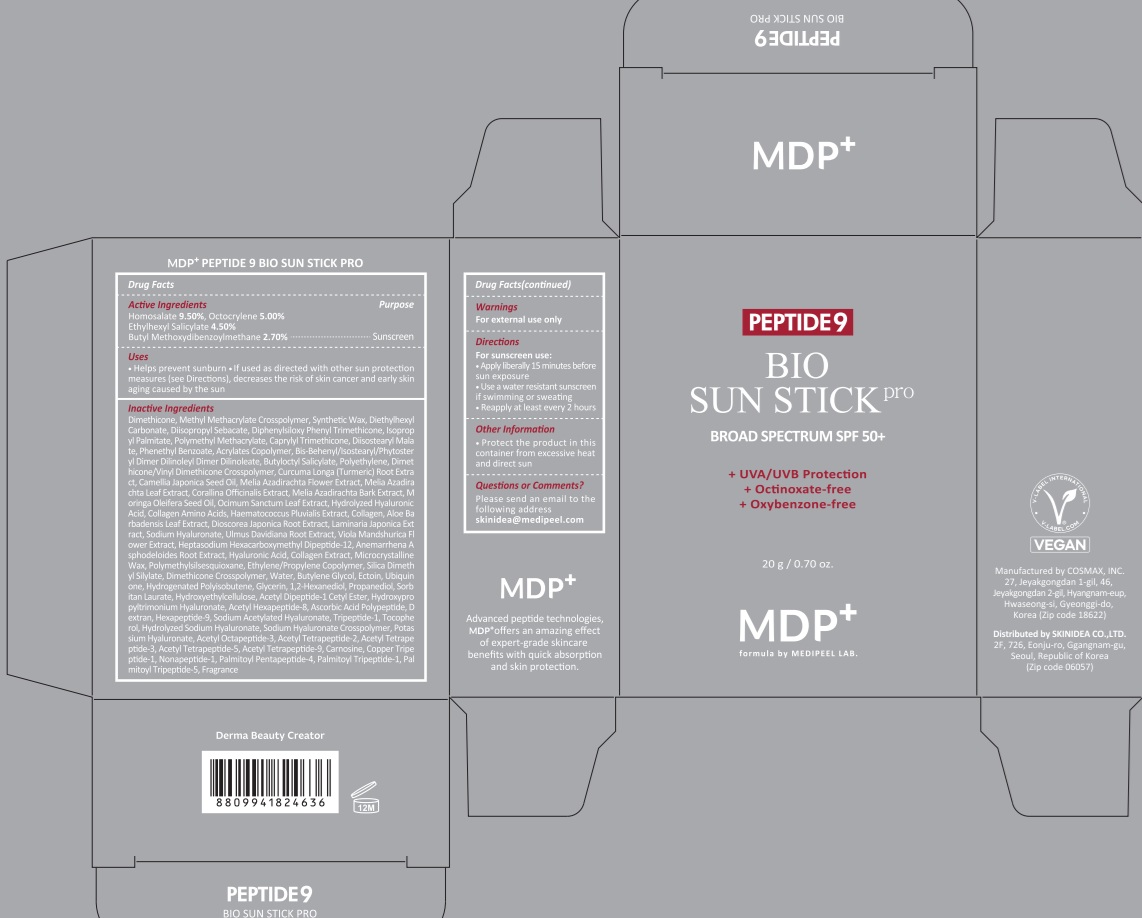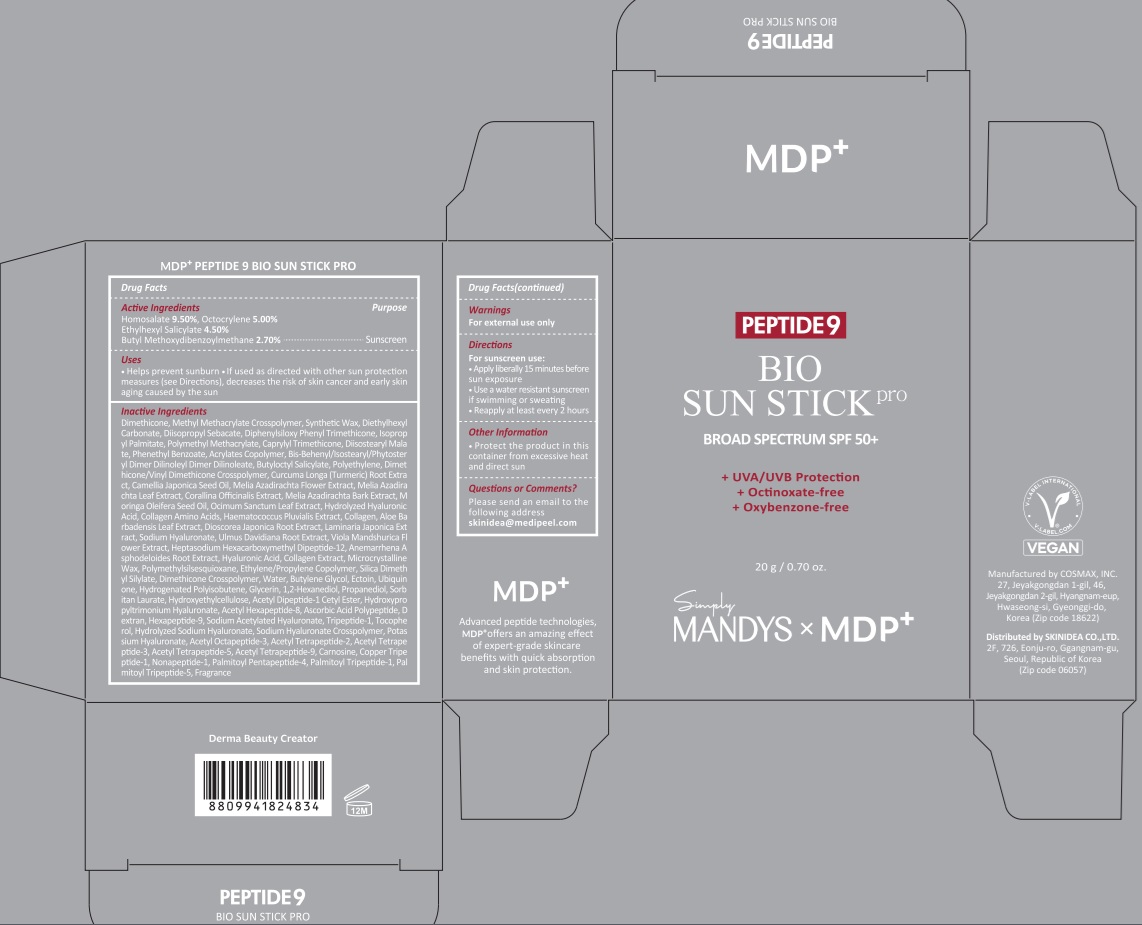 DRUG LABEL: MDP PEPTIDE 9 BIO SUN PRO
NDC: 72220-002 | Form: STICK
Manufacturer: SKINIDEA CO., LTD
Category: otc | Type: HUMAN OTC DRUG LABEL
Date: 20250609

ACTIVE INGREDIENTS: HOMOSALATE 9.5 g/100 g; OCTOCRYLENE 5 g/100 g; AVOBENZONE 2.7 g/100 g; OCTISALATE 4.5 g/100 g
INACTIVE INGREDIENTS: DIMETHICONE; DIISOPROPYL SEBACATE; DIETHYLHEXYL CARBONATE

Active ingredient(s)

Homosalate 9.50%

Octocrylene 5.00%

Ethylhexyl Salicylate 4.50%

Butyl Methoxydibenzoylmethane 2.70%

Inactive ingredients

Dimethicone, Methyl Methacrylate Crosspolymer, Synthetic Wax, Diethylhexyl Carbonate, Diisopropyl Sebacate, Diphenylsiloxy Phenyl Trimethicone, Isopropyl Palmitate, Polymethyl Methacrylate, Caprylyl Trimethicone, Diisostearyl Malate, Phenethyl Benzoate, Acrylates Copolymer, Bis-Behenyl/Isostearyl/Phytosteryl Dimer Dilinoleyl Dimer Dilinoleate, Butyloctyl Salicylate, Polyethylene, Dimethicone/Vinyl Dimethicone Crosspolymer, Microcrystalline Wax, Polymethylsilsesquioxane, Ethylene/Propylene Copolymer, Curcuma Longa (Turmeric) Root Extract, Silica Dimethyl Silylate, Dimethicone Crosspolymer, Fragrance(Parfum), Camellia Japonica Seed Oil, Melia Azadirachta Flower Extract, Melia Azadirachta Leaf Extract, Corallina Officinalis Extract, Melia Azadirachta Bark Extract, Moringa Oleifera Seed Oil, Ocimum Sanctum Leaf Extract, Water, Butylene Glycol, Hydrolyzed Hyaluronic Acid, Ectoin, Ubiquinone, Hydrogenated Polyisobutene, Glycerin, 1,2-Hexanediol, Collagen Amino Acids, Propanediol, Haematococcus Pluvialis Extract, Sorbitan Laurate, Collagen, Aloe Barbadensis Leaf Extract, Dioscorea Japonica Root Extract, Hydroxyethylcellulose, Laminaria Japonica Extract, Sodium Hyaluronate, Ulmus Davidiana Root Extract, Viola Mandshurica Flower Extract, Acetyl Dipeptide-1 Cetyl Ester, Heptasodium Hexacarboxymethyl Dipeptide-12, Hydroxypropyltrimonium Hyaluronate, Acetyl Hexapeptide-8, Anemarrhena Asphodeloides Root Extract, Ascorbic Acid Polypeptide, Dextran, Hexapeptide-9, Sodium Acetylated Hyaluronate, Tripeptide-1, Tocopherol, Hyaluronic Acid, Collagen Extract, Hydrolyzed Sodium Hyaluronate, Sodium Hyaluronate Crosspolymer, Potassium Hyaluronate, Acetyl Octapeptide-3, Acetyl Tetrapeptide-2, Acetyl Tetrapeptide-3, Acetyl Tetrapeptide-5, Acetyl Tetrapeptide-9, Carnosine, Copper Tripeptide-1, Nonapeptide-1, Palmitoyl Pentapeptide-4, Palmitoyl Tripeptide-1, Palmitoyl Tripeptide-5

Purpose

Sunscreen

Warnings

■ For external use only.

INDICATIONS AND USAGE

Use(s)

■ Helps prevent sunburn

■ If used as directed with other sun protection measures (see Directions), decreases the risk of skin cancer and early skin aging caused by the sun

Directions

For sunscreen use:

■ Apply liberally 15 minutes before sun exposure

■ Use a water-resistant sunscreen if swimming or sweating

■ Reapply at least every 2 hours

Other Information

■ Protect the product in this container from excessive heat and direct sun

Questions?

■ Please send an email to the following address
skinidea@medipeel.com